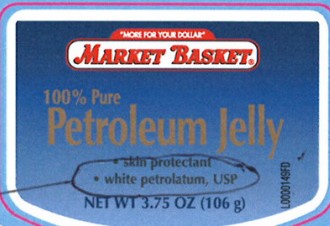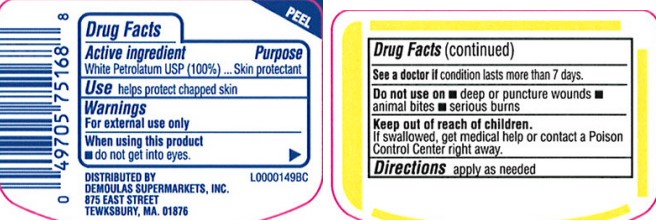 DRUG LABEL: Petroleum Skin Protectant
NDC: 53942-069 | Form: JELLY
Manufacturer: Demoulas Super Markets, Inc
Category: otc | Type: HUMAN OTC DRUG LABEL
Date: 20260203

ACTIVE INGREDIENTS: PETROLATUM 1 g/1 g

Market Basket 069.001/069AA
Petroleum Jelly

Active ingredient

White petrolatum USP (100%)

Purpose

Skin protectant

Uses

Helps protect chapped skin

Warnings

For external use only

When using this product

- do not get into eyes

See a doctor if

condition lasts more than 7 days.

Do not use

- deep or puncture wounds
- animal bites
- serious burns

Keep out of reach of children.

If swallowed, get medical help or contact a Poison Control Center right away.

Directions

apply as needed

INACTIVE INGREDIENT

none

Adverse Reactions

DISTRIBUTED BY:

DEMOULAS SUPERMARKETS, INC.

875 EAST STREET

TWEKSBURY, MA 01876

principal display panel

"MORE FOR YOUR DOLLAR"

MARKET BASKET®

100% Pure

Petroleum Jelly

- skin protectant
- white petrolatum, USP

NET WT 3.75 OZ (106 g)